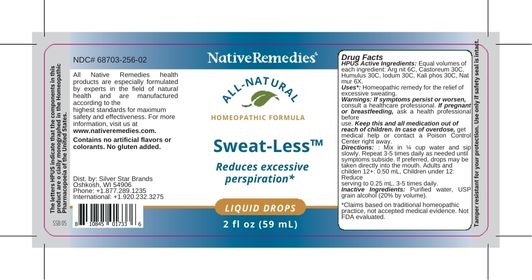 DRUG LABEL: Sweat-Less
NDC: 68703-256 | Form: LIQUID
Manufacturer: Silver Star Brands
Category: homeopathic | Type: HUMAN OTC DRUG LABEL
Date: 20250101

ACTIVE INGREDIENTS: SILVER NITRATE 6 [hp_C]/59 mL; CASTOR CANADENSIS SCENT GLAND SECRETION 30 [hp_C]/59 mL; HOPS 30 [hp_C]/59 mL; POTASSIUM PHOSPHATE, DIBASIC 30 [hp_C]/59 mL; IODINE 30 [hp_C]/59 mL; SODIUM CHLORIDE 6 [hp_X]/59 mL
INACTIVE INGREDIENTS: ALCOHOL; WATER

NativeRemedies® Sweat-Less™

HPUS Active Ingredients:

Each dose contains equal parts of: Arg nit 6C, Castoreum 30C, Humulus 30C, Iodum 30C, Kali phos 30C, Nat mur 6X.

Uses*:

Homeopathic remedy for the relief of excessive sweating.

*Claims based on traditinal homeopathic practice, not accepted medical evidence. Not FDA evaluated.

Warnings:

If symptoms persist or worsen, consult a healthcare professional. If pregnant or breastfeeding, ask a health professional before use. Keep this and all medication out of reach of children. In case of overdose, get medical help or contact a Poison Control Center right away.

Directions:

For all ages: Mix 0.50 mL in 1/4 cup water and sip slowly. Repeat 3-5 times daily as needed until symptoms subside. If preferred, drops may be taken directly into the mouth. Children under 12: Reduce serving to 0.25 mL, 3-5 times daily.

OTHER SAFETY INFORMATION

All Native Remedies health products are especially formulated by experts in the field of natural health and are manufactured according tot he highest pharmaceutical standards for maximum safety and effectiveness. For more information, visit us at www.nativeremedies.com.

Contains no animal products, gluten, artificial flavors, preservatives, or colorants. Suitable for vegetarians.

Inactive Ingredients:

Purified water, USP grain alcohol (20% by volume)

KEEP OUT OF REACH OF CHILDREN

Keep this and all medication out of reach of children. In case of overdose, get medical help or contact a Poison Control Center right away.

PREGNANCY OR BREAST FEEDING

If pregnant or breastfeeding, ask a health professional before use.

PURPOSE

Reduces excessive perspiration